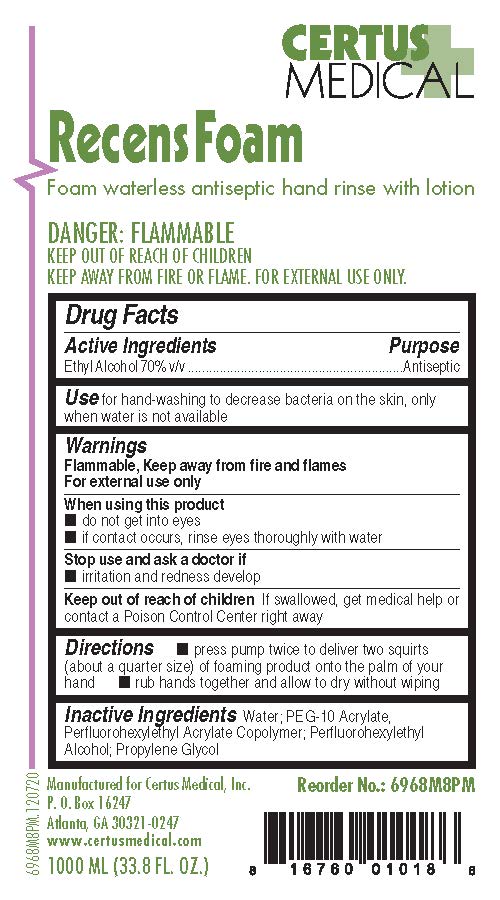 DRUG LABEL: Recens Foam
NDC: 75990-968 | Form: LIQUID
Manufacturer: Certus Medical, Inc.
Category: otc | Type: HUMAN OTC DRUG LABEL
Date: 20251120

ACTIVE INGREDIENTS: ALCOHOL 0.7 mL/1 mL
INACTIVE INGREDIENTS: PEG-10 ACRYLATE/PERFLUOROHEXYLETHYL ACRYLATE COPOLYMER; WATER; PROPYLENE GLYCOL

Recens Foam 6968 Drug Facts and Label

Drug Facts Box OTC-Active Ingredient Section

Ethyl Alcohol 70% v/v

Drug Facts Box OTC-Purpose Section

Antiseptic

Drug Facts Box OTC-Indications & Usage Section

for hand-washing to decrease bacteria on the skin, only when water is not available

Drug Facts Box OTC-Warnings Section

FLAMMABLE, keep away from fire and flames

For external use only

Drug Facts Box OTC-When Using Section

do not get into eyes

if contact occurs, rinse eyes thoroughly with water

Drug Facts Box OTC-Stop Use Section

irritation and redness develop

Drug Facts Box OTC-Keep Out of Reach of Children Section

if swallowed, get medical help or contact a Poison Control Center right away

Drug Facts Box OTC-Dosage & Administration Section

apply to hands and rub lightly until dry without wiping or rinsing

Drug Facts Box OTC-Inactive Ingredient Section

water, PEG-10 acrylate, perfluorohexylethyl acrylate copolymer, propylene glycol

Recens Foam 6968